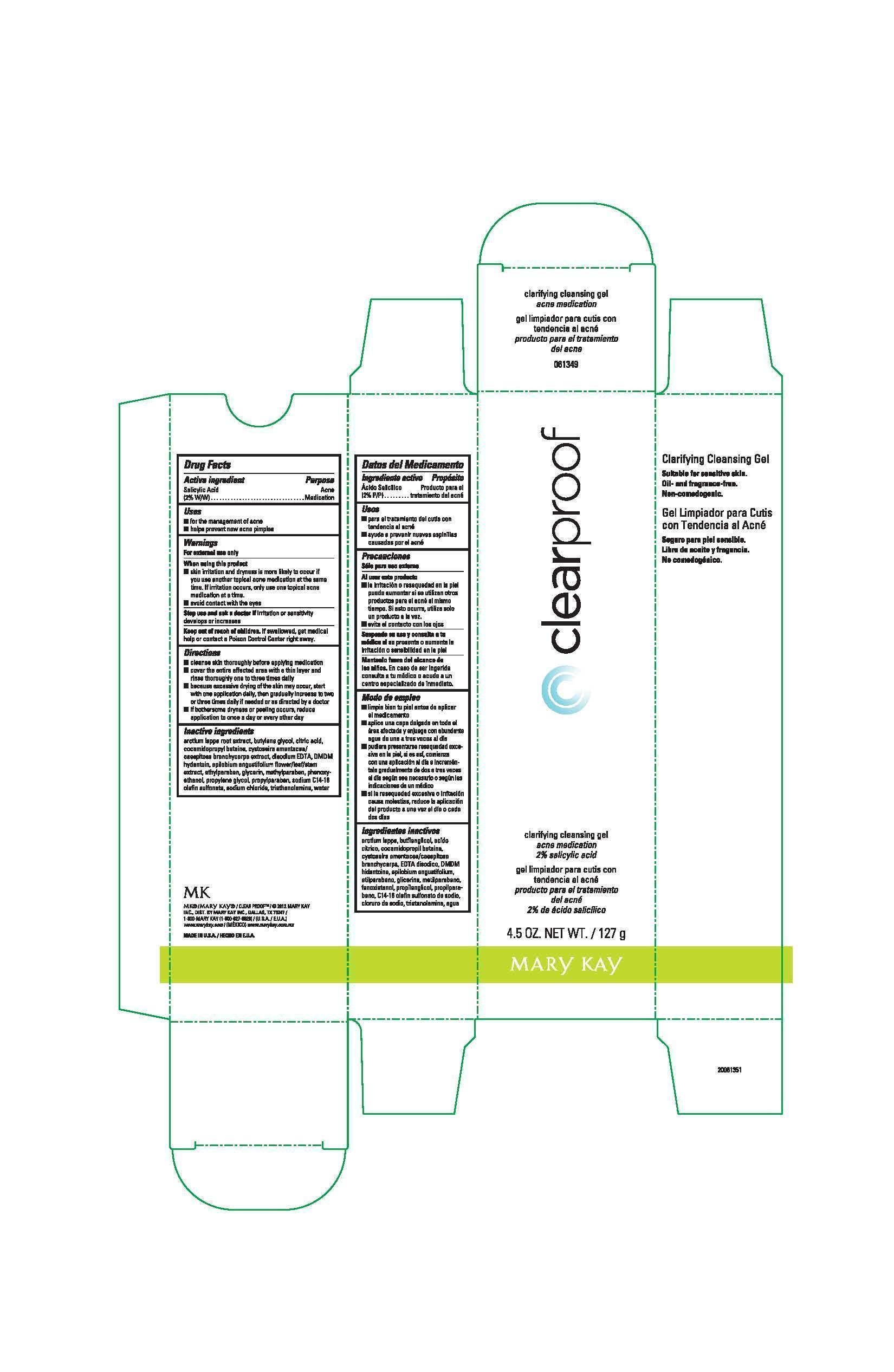 DRUG LABEL: Clear Proof Clarifying Cleansing Gel
NDC: 51531-1349 | Form: GEL
Manufacturer: Mary Kay Inc.
Category: otc | Type: HUMAN OTC DRUG LABEL
Date: 20241217

ACTIVE INGREDIENTS: SALICYLIC ACID 2 g/100 g
INACTIVE INGREDIENTS: SODIUM C14-16 OLEFIN SULFONATE; WATER; COCAMIDOPROPYL BETAINE; SODIUM CHLORIDE; TROLAMINE; EDETATE DISODIUM; PHENOXYETHANOL; BUTYLENE GLYCOL; CITRIC ACID MONOHYDRATE; PROPYLENE GLYCOL; METHYLPARABEN; ETHYLPARABEN; DMDM HYDANTOIN; ARCTIUM LAPPA ROOT; PROPYLPARABEN; GLYCERIN; EPILOBIUM ANGUSTIFOLIUM FLOWERING TOP

Clear Proof Clarifying Cleansing Gel
Drug Facts

Active ingredient

Salicylic Acid (2% W/W)

Purpose

Acne Medication

Uses

- for the management of acne
- helps prevent new acne pimples

Warnings

For external use only

When using this product

- skin irritation and dryness is more likely to occur if you use another topical acne medication at the same time. If irritation occurs, only use one topical acne medication at a time.
- avoid contact with the eyes

Stop use and ask a doctor if

irritation or sensitivity develops or increases

Keep out of reach of children.

If swallowed, get medical help or contact a Poison Control Center right away.

Directions

- cleanse skin thoroughly before applying medication
- cover the entire affected area with a thin layer and rinse thoroughly one to three times daily
- because excessive drying of the skin may occur, start with one application daily, then gradually increase to two or three times daily if needed or as directed by a doctor
- if bothersome dryness or peeling occurs, reduce application to once a day or every other day

Inactive ingredients

arctium lappa root extract, butylene glycol, citric acid, cocamidopropyl betaine, cystoseira amentacea/caespitosa branchycarpa extract, disodium EDTA, DMDM hydantoin, epilobium angustifolium flower/leaf/stem extract, ethylparaben, glycerin, methylparaben, phenoxyethanol, propylene glycol, propylparaben, sodium C14-16 olefin sulfonate, sodium chloride, triethanolamine, water

Principal Display Panel - 127 g carton

clearproof

clarifying cleansing gel

acne medication

2% salicylic acid

4.5 OZ. NET WT. / 127 g

Mary Kay